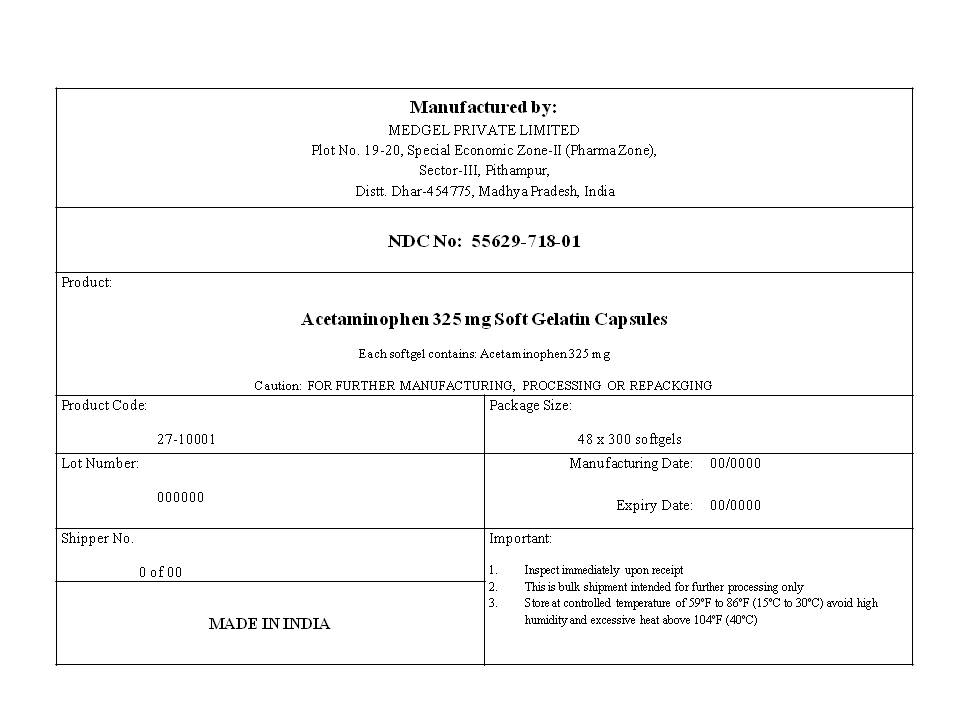 DRUG LABEL: ACETAMINOPHEN (RED)
NDC: 55629-718 | Form: CAPSULE, LIQUID FILLED
Manufacturer: One2zee Limited Liability Company
Category: otc | Type: HUMAN OTC DRUG LABEL
Date: 20190222

ACTIVE INGREDIENTS: ACETAMINOPHEN 325 mg/1 1
INACTIVE INGREDIENTS: PROPYLENE GLYCOL; POVIDONE K30; FD&C RED NO. 40; TITANIUM DIOXIDE; POLYETHYLENE GLYCOL 400; GELATIN; GLYCERIN; SORBITOL; WATER

ACETAMINOPHEN

Drug Facts

Active ingredient (in each capsule)

Acetaminophen 325 mg

Purpose

Pain reliever/ fever reducer

Uses

• Temporarily relieves minor aches and pains due to :

◦ headache
◦ muscular aches
◦ backache
◦ minor pain of arthritis
◦ the common cold
◦ toothache
◦ premenstrual and menstrual cramps

• Temporarily reduces fever

Warnings

Liver warning: This product contains acetaminophen. The maximum daily dose of this product is 10 softgels (3,250 mg) in 24 hours for adults or 5 softgels (1,625 mg) in 24 hours for children. Severe liver damage may occur if
• adult takes more than 4,000 mg of acetaminophen in 24 hours
• child takes more than 5 doses in 24 hours, which is the maximum daily amount
• taken with other drugs containing acetaminophen
• adult has 3 or more alcoholic drinks every day while using this product

Do not use

- with any other drug containing acetaminophen (prescription or nonprescription). If you are not sure whether a drug contains acetaminophen, ask a doctor or pharmacist
- if you are allergic to acetaminophen or any of the inactive ingredients in this product

Ask a doctor before use if the user has liver disease

Ask a doctor or pharmacist before use if the user is taking the blood thinning drug warfarin

Stop use and ask a doctor if

- pain gets worse or lasts more than 10 days in adults
- pain gets worse or lasts more than 5 days in children under 12 years
- fever gets worse or lasts more than 3 days
- new symptoms occur
- redness or swelling is present

These could be signs of a serious condition.

PREGNANCY OR BREAST FEEDING

If pregnant or breast-feeding, ask a health professional before use.

Keep out of reach of children.

Overdose warning

In case of overdose, get medical help or contact a Poison Control Center right away. (1-800-222-1222) Quick medical attention is critical for adults as well as for children even if you do not notice any signs or symptoms.

Directions

Do not take more than directed
(see Overdose warning)

adults and children 12 years and over | - take 2 softgels every 4 to 6 hours while symptoms last - do not take more than 10 softgels in 24 hours - do not use for more than 10 days unless directed by a doctor
children 6-11 years | - take 1 softgel every 4 to 6 hours while symptoms last - do not take more than 5 softgels in 24 hours - do not use for more than 5 days unless directed by a doctor
children under 6 years | ask a doctor

Other Information

store at room temperature 15°-30°C (59°-86°F) and avoid excessive heat

Inactive ingredients

FD&C red #40, gelatin, sorbitol, glycerin, polyethylene glycol 400, povidone K-30, propylene glycol, titanium dioxide, purified water

PRINCIPAL DISPLAY PANEL - Shipping Label

ACETAMINOPHEN CAPSULES, 325 mg

Quantity : 48 Bags of 300 Capsules each
NDC. No : 55629-718-01

Important:

1. Inspect immediately upon receipt

2. This is bulk shipment intended for further processing only
3. Store at controlled temperature of 59°F to 86°F (15°C to 30°C) avoid high humidity and excessive heat above 104°F (40°C)